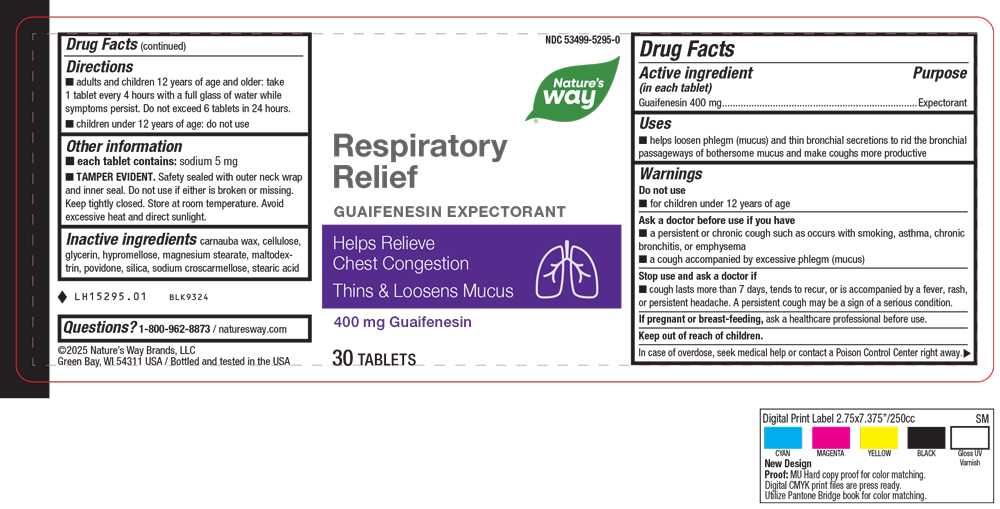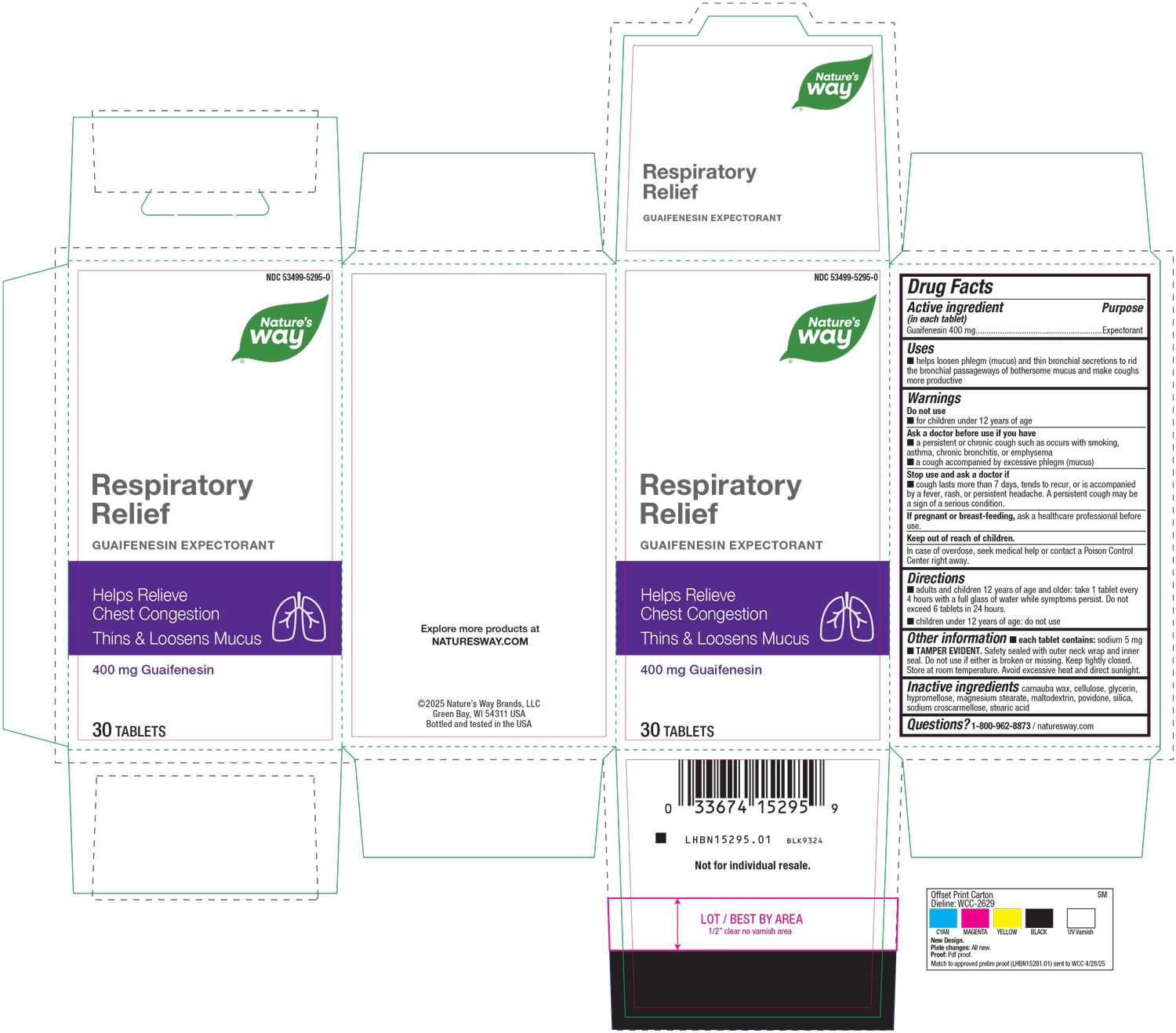 DRUG LABEL: Respiratory Relief
NDC: 53499-5295 | Form: TABLET
Manufacturer: Schwabe North America, Inc
Category: otc | Type: HUMAN OTC DRUG LABEL
Date: 20250729

ACTIVE INGREDIENTS: GUAIFENESIN 400 mg/1 1
INACTIVE INGREDIENTS: CARNAUBA WAX; MICROCRYSTALLINE CELLULOSE; GLYCERIN; HYPROMELLOSE, UNSPECIFIED; MAGNESIUM STEARATE; MALTODEXTRIN; POVIDONE; SILICON DIOXIDE; CROSCARMELLOSE SODIUM; STEARIC ACID

Respiratory Relief

Active Ingredient

Guaifenesin 400 mg

Inactive Ingredients

Carnauba Wax

Cellulose

Glycerin

Hypromellose

Magnesium Stearate

Maltodextrin

Povidone

Silica

Sodium Croscarmellose

Stearic Acid

Dosage & Administration

Adults & children 12 years of age and older: take 1 tablet every 4 hours with a full glass of water while symptoms persist. Do not to exceed 6 tablets in 24 hours.

Children under 12 years of age: do not use.

Purpose

Helps loosen phlegm (mucus) and thin bronchial secretions to rid the bronchial passageways of bothersome mucus and make coughs more productive.

Indications & Usage

Helps loosen phlegm (mucus) and thin bronchial secretions to rid the bronchial passageways of bothersome mucus and make coughs more productive.

Warnings

Do not use for children under 12 years of age.

Ask a doctor before use if you have a persistent or chronic cough such as occurs with smoking, asthma, chronic bronchitis, or emphysema, a cough accompanied by excessive phlegm (mucus).

Stop Use

Stop use and ask a doctor if cough lasts more than 7 days, tends to recur, or is accompanied by a fever, rash or persisient headache.

A persistent cough may be a sign of a serious condition.

Keep out of Reach of Children

Pregnant or Breast Feeding

If pregnant or breast-feeding, ask a healthcare professional before use.

Overdosage:

In case of overdose, seek medical help or contact a Poison Control Center right away.